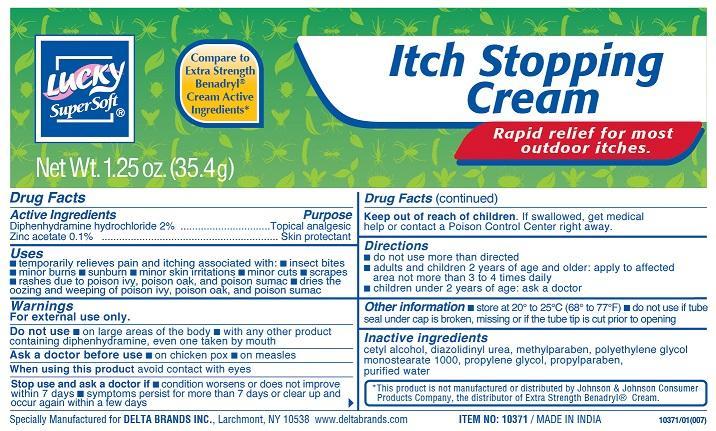 DRUG LABEL: Savvy
NDC: 83650-102 | Form: CREAM
Manufacturer: Savvy Care and Cosmetics
Category: otc | Type: HUMAN OTC DRUG LABEL
Date: 20241219

ACTIVE INGREDIENTS: DIPHENHYDRAMINE HYDROCHLORIDE 2 g/100 g; ZINC ACETATE 0.1 g/100 g
INACTIVE INGREDIENTS: CETYL ALCOHOL; DIAZOLIDINYL UREA; METHYLPARABEN; PROPYLENE GLYCOL; PROPYLPARABEN; WATER; POLYETHYLENE GLYCOL, UNSPECIFIED

ITCH STOPPING CREAM

Active Ingredient

Diphenhydramine hydrochloride 2%

Zinc acetate 0.1%

Purpose

Topical analgesic

Skin protectant

Uses

■ temporarily relieves pain and itching associated with ■ insect bites ■ minor burns ■ sunburn ■ minor skin irritations ■ minor cuts ■ scrapes ■ rashes due to poison ivy, poison oak, and poison sumac ■ dries the oozing and weeping of poison ivy, poison oak, and poison sumac

Warnings

For external use only

Do not use

■ on large areas of the body ■ with any other product containing diphenhydramine, even one taken by mouth

Ask a doctor before use■ on chicken pox ■ on measles

Ask a doctor before use

avoid contact with eyes

Stop use and ask a doctor if

■ condition worsens, or does not improve within 7 days ■ symptoms persist for more than 7 days or clear up and occur again wihin a few days

Keep out of reach of children

If swallowed, get medical help or contact a Poison Control Center right away

Directions

■ do not use more than directed

■ adults and children2 years of age and older: apply to affected area not more than 3 to 4 times daily ■ children under 2 years of age: ask a doctor

Other information

■ store at 20 to 25C (68-77F) ■ do not use if tube seal under cap is broken, missing or if the tube tip is cut prior to opening

Inactive Ingredients

cetyl alcohol, diazolidinyl urea, methylparaben, propylene glycol monostearate 1000, propylene glycol, propylparaben, purified water